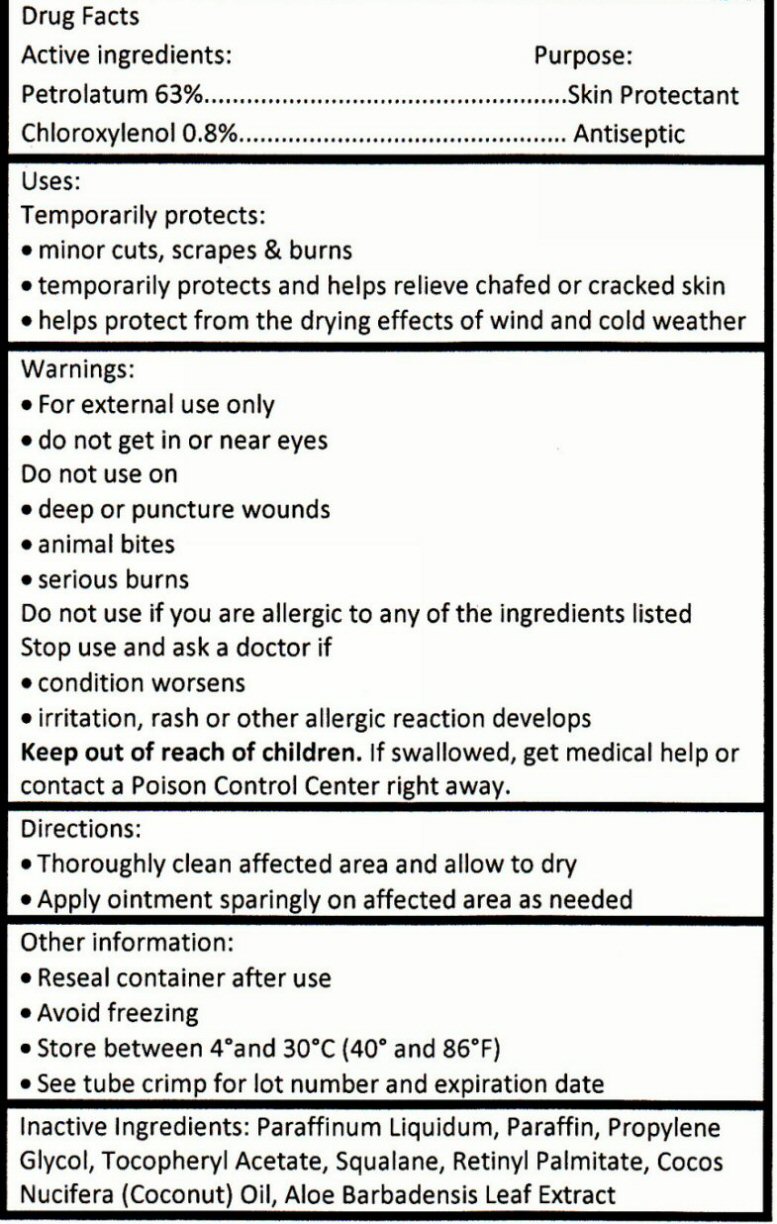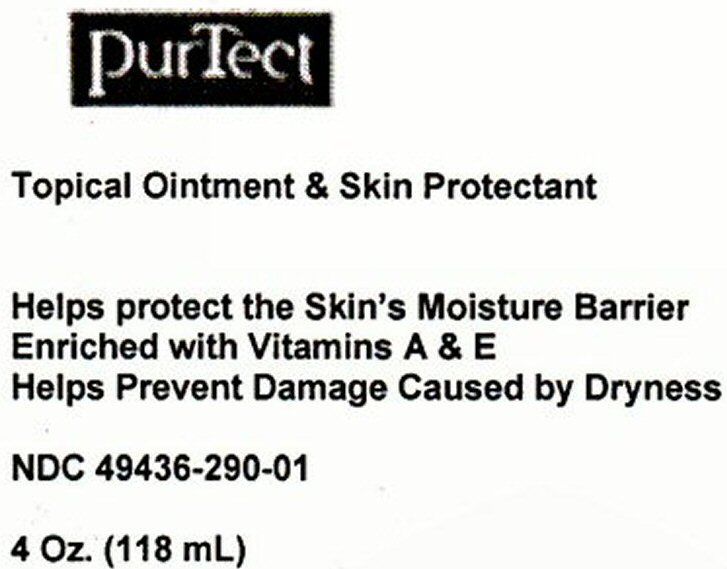 DRUG LABEL: PurTect
NDC: 49436-290 | Form: OINTMENT
Manufacturer: PurKlenz Formulations Inc.
Category: otc | Type: HUMAN OTC DRUG LABEL
Date: 20120515

ACTIVE INGREDIENTS: PETROLATUM 63 mL/100 mL; CHLOROXYLENOL 0.8 mL/100 mL
INACTIVE INGREDIENTS: MINERAL OIL; PARAFFIN; PROPYLENE GLYCOL; ALPHA-TOCOPHEROL ACETATE; SQUALANE; VITAMIN A PALMITATE; COCONUT OIL; ALOE VERA LEAF

Active Ingredients

Drug Facts

Active ingredients

Petrolatum 63% Chloroxylenol 0.8%

Purpose

Skin Protectant Antiseptic

Keep out of reach of children. If swallowed, get medical help or contact a Poison Control Center right away.

Uses

Temporarily protects:

- minor cuts, scrapes and burns
- temporarily protects and helps relieve chafed or cracked skin
- help protects from the drying effects of wind and cold weather

Warnings

- For external use only
- do not get near eyes

Do not use on

- deep puncture wounds
- animal bites
- serious burns

Do not use if you are allergic to any ingredients listed
Stop use and ask a doctor if

- condition worsens
- irritation, rash or other allergic reaction develops

Directions

- Thoroughly clean affected area and allow to dry
- Apply ointment sparingly on affected area as needed

Other Information

- Reseal container after use
- Avoid freezing
- Store between 4 degrees and 30 degrees C (40 degrees and 86 degrees F)
- See tube crimp for lot number and expiration date

Inactive Ingredients

Inactive Ingredients: Paraffium Liquidum, Paraffin, Propylene Glycol, Tocopheryl Acetate, Squalane, Retinyl Palmitate, Cocos Nucifera (Coconut) Oil, Aloe Barbadensis Leaf Extract

Package Label

PurTect

Topical Ointment and Skin Protectant

Helps protect the Skin's Moisture Barrier

Enriched with Vitamins A and E

Helps Prevent Damage Caused by Dryness

4 Fl. Oz (118 mL)

NDC 49436-xxx-xx

Made in Canada Distributed in the U.S.A. by PurKlenz Formulations Inc.

Questions or comments? www.purklenz.com